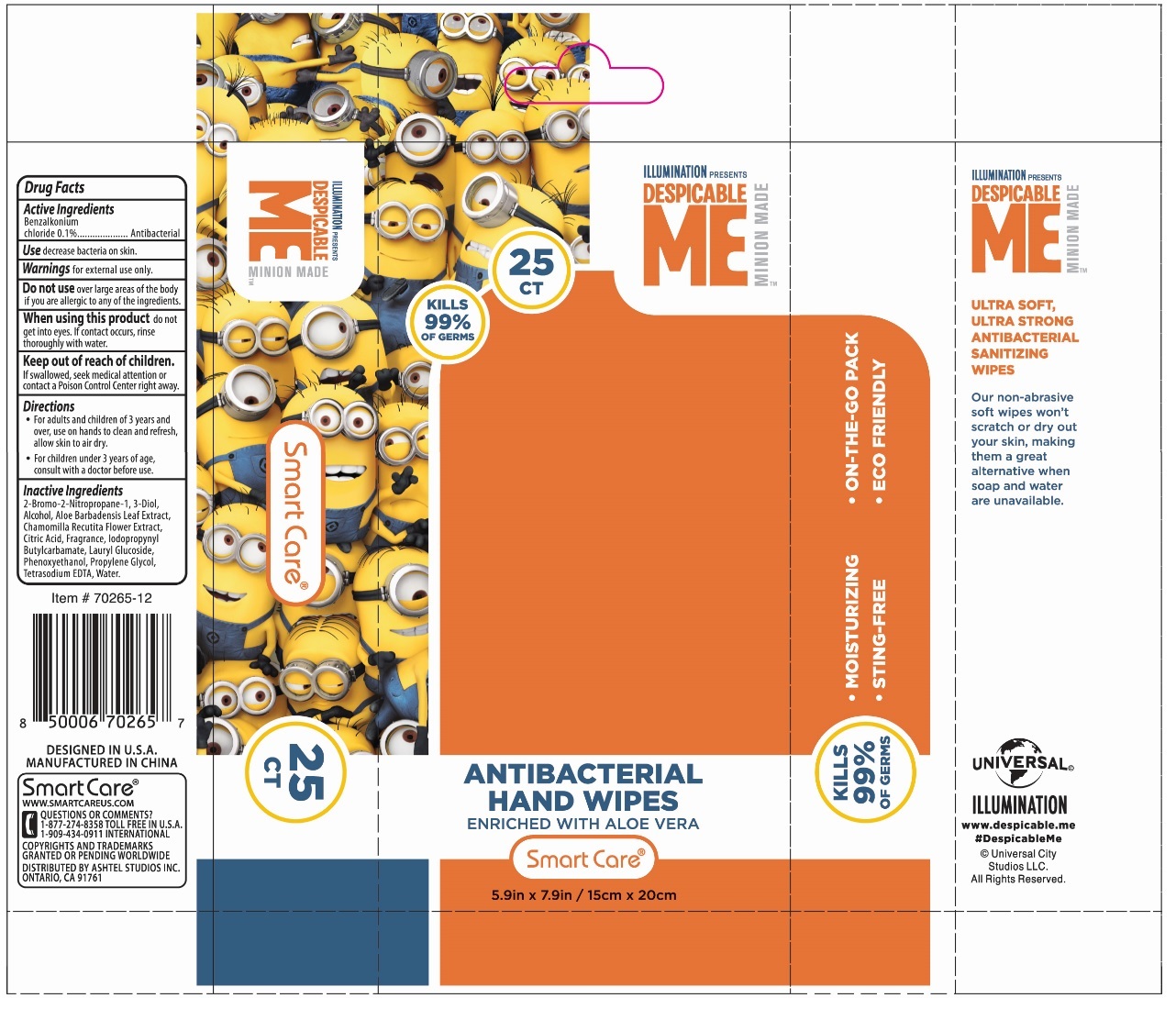 DRUG LABEL: MINIONS ANTIBACTERIAL HAND WIPES
NDC: 70108-019 | Form: CLOTH
Manufacturer: Ashtel Studios, Inc.
Category: otc | Type: HUMAN OTC DRUG LABEL
Date: 20230109

ACTIVE INGREDIENTS: BENZALKONIUM CHLORIDE 0.1 g/100 g
INACTIVE INGREDIENTS: BRONOPOL; ALCOHOL; ALOE VERA LEAF; CHAMOMILE; CITRIC ACID MONOHYDRATE; IODOPROPYNYL BUTYLCARBAMATE; LAURYL GLUCOSIDE; PHENOXYETHANOL; PROPYLENE GLYCOL; EDETATE SODIUM; WATER

MINIONS ANTIBACTERIAL HAND WIPES

Active Ingredients

Benzalkonium chloride 0.1%

Purpose

Antibacterial

Use

decrease bacteria on skin.

Warnings

for external use only.

Do not use over large area of the body if you are allergic to any of the ingredients.

When using this product do not get into eyes. If contact occurs, rinse thoroughly with water.

Keep out of reach of children.

If swallowed, seek medical attention or contact a Poison Control Center right away.

Directions

- For adults and children of 3 years and over, use on hands to clean and refresh, allow skin to air dry.
- For children under 3 years of age, consult with a doctor before use.

Inactive Ingredients

2-Bromo-2-Nitropropane-1, 3-Diol, Alcohol, Aloe Barbadensis Leaf Extract, Chamomilla Recutita Flower Extract, Citric Acid, Fragrance, Iodopropynyl Butylcarbamate, Lauryl Glucoside, Phenoxyethanol, Propylene Glycol, Tetrasodium EDTA, Water.

DESPICABLE ME

™MINION MADE

ENRICHED WITH ALOE VERA

KILLS 99% OF GERMS

- MOISTURIZING
- STING-FREE
- ON-THE-GO-PACK
- ECO FRIENDLY

ULTRA SOFT, ULTRA STRONG ANTIBACTERIAL SANITIZING WIPES

Our non-abrasive soft wipes won't scratch or dry out your skin, making them a great alternative when soap and water are unavailable.

DESIGNED IN U.S.A.
MANUFACTURED IN CHINA

Smart Care®
WWW.SMARTCAREUS.COM

QUESTIONS OR COMMENTS?
1-877-274-8358 TOLL FREE IN U.S.A
1-909-434-0911 INTERNATIONAL

DISTRIBUTED BY ASHTEL STUDIOS INC.
ONTARIO, CA 91761